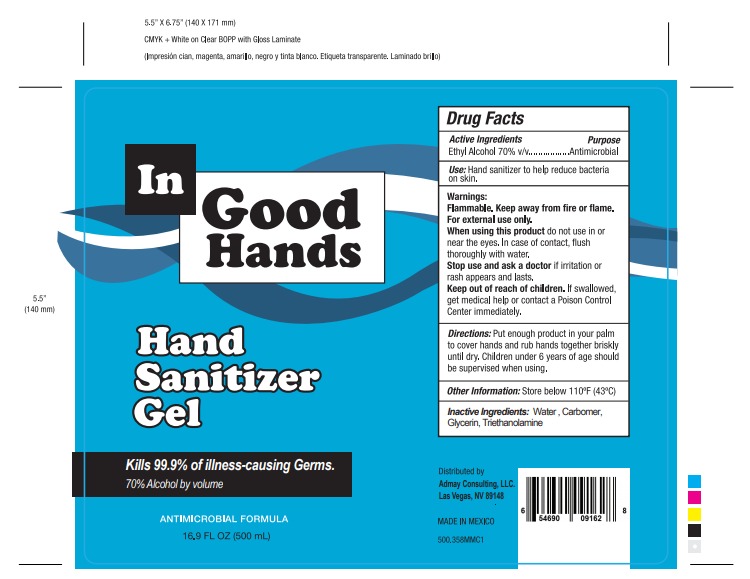 DRUG LABEL: IN GOOD HANDS
NDC: 78501-3000 | Form: GEL
Manufacturer: COMERCIAL GOURA,S. DE R.L.
Category: otc | Type: HUMAN OTC DRUG LABEL
Date: 20200607

ACTIVE INGREDIENTS: ALCOHOL 0.7 mL/1 mL
INACTIVE INGREDIENTS: TRIETHANOLAMINE CAPROYL GLUTAMATE 0.002 mL/1 mL; CARBOMER 940 0.002 mL/1 mL; WATER 0.2585 mL/1 mL; GLYCERIN 0.0375 mL/1 mL

HAND SANITIZER GEL IN GOOD HANDS

DOSAGE AND ADMINISTRATION

Place enough product on hands to cover all surfaces. Rub hands together until dry.

INACTIVE INGREDIENTS

Inactive ingredients Water (Aqua), Glycerin, Carbomer, Triethanolamine

DIRECTIONS

Place enough product on hands to cover all surfaces. Rub hands together until dry.

Keep out of reach of children. If swallowed, get medical help or contact a Poison Control Center right away.

PURPOSE

Purpose Antmicrobial

WARNINGS AND PRECAUTIONS

Store below 110°F (43°C)

Children under 6 years of age should be supervised when using.

WARNINGS

For external use only. Flammable. Keep away from heat or flame

ACTIVE INGREDIENT

Active ingredient. Ethyl Alcohol 70% v/v